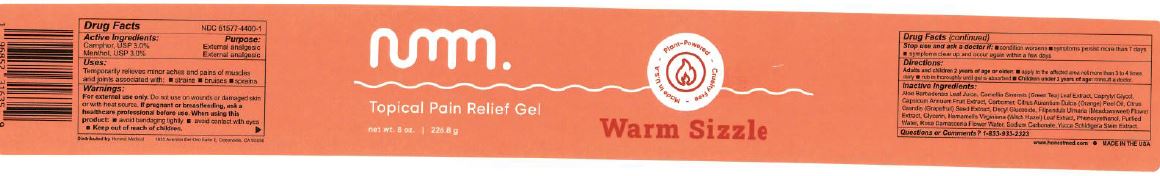 DRUG LABEL: NUMM WARM SIZZLE
NDC: 61577-4400 | Form: GEL
Manufacturer: SOMBRA COSMETICS INC.
Category: otc | Type: HUMAN OTC DRUG LABEL
Date: 20231011

ACTIVE INGREDIENTS: CAMPHOR (SYNTHETIC) .03 g/1 g; MENTHOL .03 g/1 g
INACTIVE INGREDIENTS: WATER; CARBOMER HOMOPOLYMER TYPE C; GLYCERIN; ALOE VERA LEAF; DECYL GLUCOSIDE; YUCCA SCHIDIGERA ROOT; CAPSICUM; GREEN TEA LEAF; FILIPENDULA ULMARIA FLOWER; GRAPEFRUIT SEED OIL; WITCH HAZEL; ORANGE OIL; ROSA CENTIFOLIA FLOWER OIL; PHENOXYETHANOL; CAPRYLYL GLYCOL; SODIUM CARBONATE

Numm Warm Sizzle Tpoical Pain Relief Gel

Active Ingredients

Camphor 3%, Menthol 3%

Purpose

Purpose External Analgesic

Keep out of reach of childern

Uses

Temporarily relieves minor aches and pains of muscles and joints with: simple backaches,strains, bruises, and sprains

Warnings

For external use only. Do not use on wounds or damaged skin. When using this product: avoid bandaging tightly, avoid contact with eyes, keep out of reach of children.

Stop use and ask doctor if: condition worsens, symptoms persist for more than 7 days, clear up and occur again within a few days.

Directions

adults and children 2 years of age and older: apply to affected area not more than 3 to 4 times daily, rub in thoroughly until gel is absorbed, children under 2 years of age: consult a doctor.

Inactive Ingredients

aloe barbadensis leaf juice,camellia sinensis (green tea) leaf extract, caprylyl glycol, capsicum annuum fruit extract, carbomer, citrus aurntium dulcis (orange) peel oil, citrus grandis (grapefruit) seed extract, decyl glucoside, filipendula ulmaria flower (queen of the prairie) extract, glycerin, hamamelis virginiana (witch hazel) leaf extract, phenoxyethanol, purified water, rosa damascena flower water, sodium carbornate, yucca schidigera stem extract,

Question or comments

1-800-225-3963